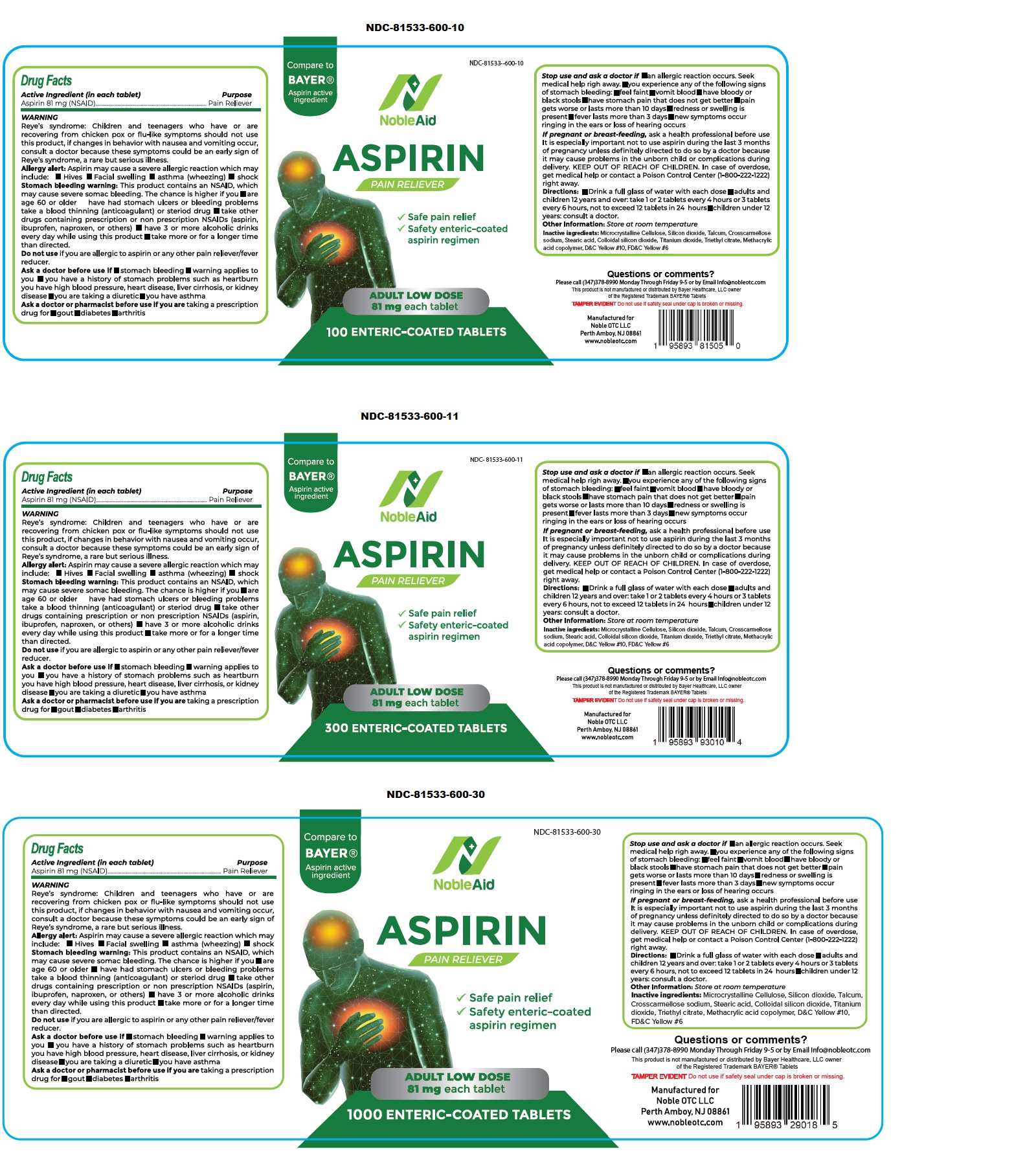 DRUG LABEL: NobleAid PAIN RELIEVER
NDC: 81533-600 | Form: TABLET, DELAYED RELEASE
Manufacturer: Noble Otc LLC
Category: otc | Type: HUMAN OTC DRUG LABEL
Date: 20241218

ACTIVE INGREDIENTS: ASPIRIN 81 mg/1 1
INACTIVE INGREDIENTS: MICROCRYSTALLINE CELLULOSE; SILICON DIOXIDE; TALC; CROSCARMELLOSE SODIUM; STEARIC ACID; TITANIUM DIOXIDE; TRIETHYL CITRATE; METHACRYLIC ACID AND ETHYL ACRYLATE COPOLYMER; D&C YELLOW NO. 10; FD&C YELLOW NO. 6

NobleAid ASPIRIN PAIN RELIEVER

Active Ingredient (in each tablet)

Aspirin 81 mg (NSAID)

Purpose

Pain Reliever

Uses

For the temporary relief of minor aches and pains

WARNING

Reye's syndrome: Children and teenagers who have or are recovering from chicken pox or flu-like symptoms should not use this product, if changes in behavior with nausea and vomiting occur, consult a doctor because these symptoms could be an early sign of Reye's syndrome, a rare but serious illness.

Allergy alert: Aspirin may cause a severe allergic reaction which may include: • Hives • Facial swelling • asthma (wheezing) • shock

Stomach bleeding warning: This product contains an NSAID, which may cause severe stomach bleeding. The chance is higher if you • are age 60 or older • have had stomach ulcers or bleeding problems take a blood thinning (anticoagulant) or steroid drug • take other drugs containing prescription or non prescription NSAIDs (aspirin, ibuprofen, naproxen, or others) • have 3 or more alcoholic drinks every day while using this product •take more or for a longer time than directed.

Do not use if you are allergic to aspirin or any other pain reliever/fever reducer.

Ask a doctor before use if •stomach bleeding •warning applies to you •you have a history of stomach problems such as heartburn you have high blood pressure, heart disease, liver cirrhosis, or kidney disease •you are taking a diuretic •you have asthma

Ask a doctor or pharmacist before use if you are taking a prescription drug for •gout •diabetes •arthritis

Stop use and ask a doctor if •an allergic reaction occurs. Seek medical help right away. •you experience any of the following signs of stomach bleeding: •feel faint •vomit blood •have bloody or black stools •have stomach pain that does not get better •pain gets worse or lasts more than 10 days •redness or swelling is present •fever lasts more than 3 days •new symptoms occur ringing in the ears or loss of hearing occurs

If pregnant or breast-feeding, ask a health professional before use. It is especially important not to use aspirin during the last 3 months of pregnancy unless definitely directed to do so by a doctor because it may cause problems in the unborn child or complications during delivery.

KEEP OUT OF REACH OF CHILDREN. In case of overdose, get medical help or contact a Poison Control Center (1-800-222-1222) right away.

Directions:

•Drink a full glass of water with each dose •adults and children 12 years and over: take 1 or 2 tablets every 4 hours or 3 tablets every 6 hours, not to exceed 12 tablets in 24 hours •children under 12 years: consult a doctor.

Other Information:

Store at room temperature

Inactive ingredients:

Microcrystalline Cellulose, Silicon dioxide, Talcum, Croscarmellose sodium, Stearic acid, Colloidal silicon dioxide, Titanium dioxide, Triethyl citrate, Methacrylic acid copolymer, D&C Yellow #10, FD&C Yellow #6

• Safe pain relief

• Safety enteric-coated aspirin regimen

ADULT LOW DOSE

Compare to Bayer® Aspirin active ingredient

Questions or comments?

Please call (347)378-8990 Monday Through Friday 9-5 or by Email Info@nobleotc.com

This product is not manufactured or distributed by Bayer Healthcare, LLC owner of the Registered Trademark BAYER® Tablets

TAMPER EVIDENT Do not use if safety seal under cap is broken or missing.

Manufactured for

Noble OTC LLC

Perth Amboy, NJ 08861

www.nobleotc.com